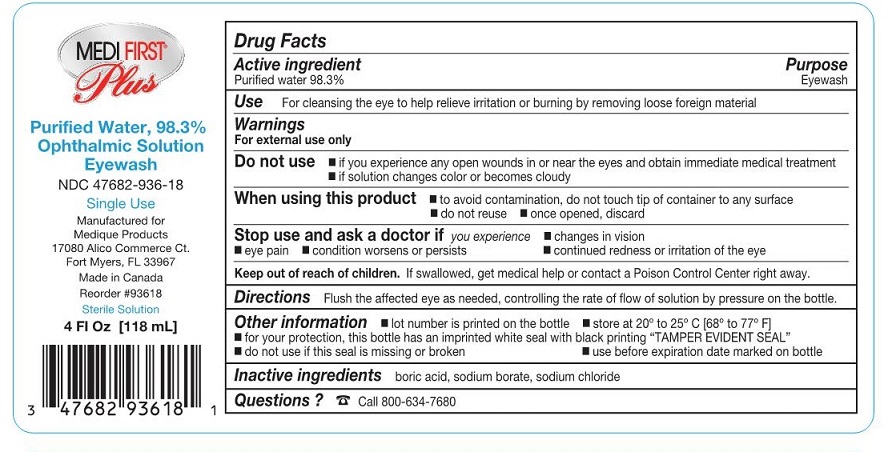 DRUG LABEL: Medi-First Plus First Aid Eye Wash
NDC: 47682-936 | Form: SOLUTION
Manufacturer: Unifirst First Aid Corporation
Category: otc | Type: HUMAN OTC DRUG LABEL
Date: 20250908

ACTIVE INGREDIENTS: WATER 0.983 mg/1 mL
INACTIVE INGREDIENTS: BORIC ACID; SODIUM BORATE; SODIUM CHLORIDE

Medi-First Plus Eye Wash

Drug Facts

Active ingredient

Purified water 98.3%

Purpose

Eyewash

Use

For cleansing the eye to help relieve irritation or burning by removing loose foreign material.

Warnings

For external use only

Do not use

- if you experience any open wounds in or near the eyes and obtain immediate medical treatment
- if solution changes color or becomes cloudy

When using this product

- to avoid contamination, do not touch tip of container to any surface
- do not reuse
- once opened, discard

Stop use and ask a doctor if

you experience

- eye pain
- changes in vision
- continued redness or irritation of the eye
- condition worsens or persists

Keep out of reach of children. If swallowed, get medical help or contact a Poison Control Center right away.

Directions

Flush the affected eye as needed, controlling the rate of flow of solution by pressure on the bottle.

Other information

- for your protection, this bottle has an imprinted white seal with black printing “TAMPER EVIDENT SEAL”
- do not use if this seal is missing or broken
- use before expiration date marked on bottle
- lot number is printed on the bottle
- store at 20º to 25º C [68º to 77º F]

Inactive ingredients

boric acid, sodium borate, sodium chloride

Questions?

Call 800-634-7680

Medi-First Plus Niagara Eye Wash Label

Medi-First® Plus
Purified Water, 98.3%

Ophthalmic Solution

Eyewash

ndc 47682-936-18
Single Use
Manufactured for Medique Products
17080 Alico Commerce Ct.

Fort Myers, FL 33967

Made in Canada

Reorder #93618

Sterile Solution
4 Fl Oz (118 mL]